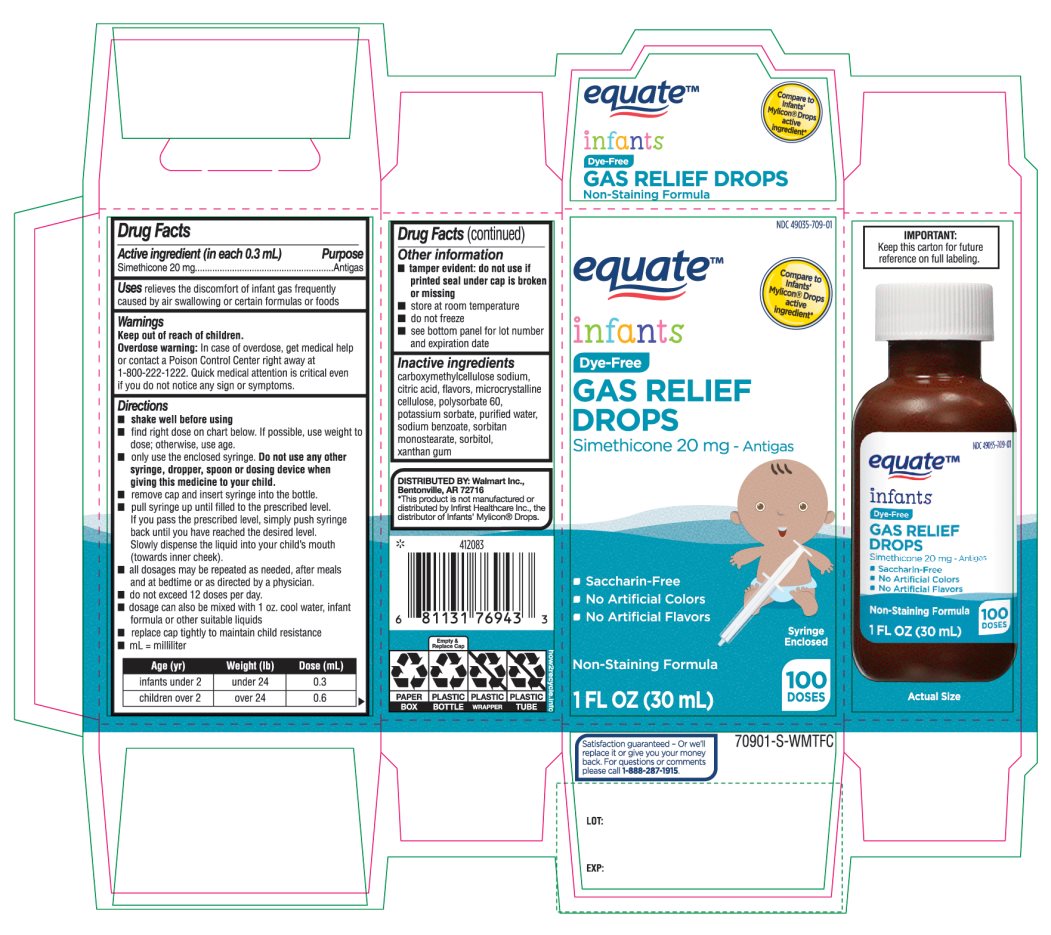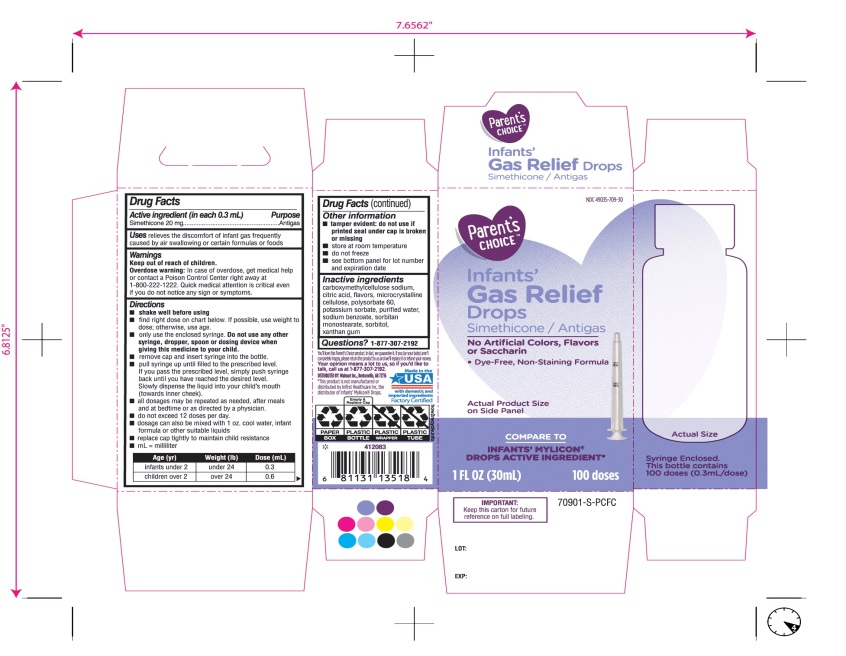 DRUG LABEL: Infants Gas Relief Drops
NDC: 49035-709 | Form: EMULSION
Manufacturer: Wal-Mart Stores,Inc.,
Category: otc | Type: HUMAN OTC DRUG LABEL
Date: 20251027

ACTIVE INGREDIENTS: DIMETHICONE, UNSPECIFIED 20 mg/0.3 mL
INACTIVE INGREDIENTS: CARBOXYMETHYLCELLULOSE SODIUM, UNSPECIFIED; ANHYDROUS CITRIC ACID; MICROCRYSTALLINE CELLULOSE; POLYSORBATE 60; POTASSIUM SORBATE; WATER; SODIUM BENZOATE; SORBITAN MONOSTEARATE; SORBITOL; XANTHAN GUM

Infants’ Gas Relief Drops Simethicone/Antigas 1 FL.OZ. (30 mL)

Active ingredient (in each 0.3 mL)

Simethicone 20 mg

Purpose

Antigas

Uses

relieves the discomfort of infant gas frequently caused by air swallowing or certain formulas or foods

Directions

- shake well before using
- find right dose on chart below. if possible, use weight to dose; otherwise use age.
- Only use the enclosed syringe. Do not use any other syringe, dropper, spoon or dosing device when giving this medicine to your child.
- remove cap and insert syringe into the prescribed level.
- pull syringe up until filled to the prescribed level. If you pass the prescribed level, simply push syringe back until you have reached the desired level.
  slowly dispense the liquid into your child’s mouth (towards inner chick.
- all dosages may be repeated as needed, after meals and at bedtime or as directed by a physician.
- do not exceed 12 doses per day.
- dosage can also be mixed with 1 oz. cool water, infant formula or other suitable liquids
- replace cap tightly to maintain child resistance
- mL= milliliter

Age (yr) | Weight (lb) | Dose(mL)
infants under 2 | under 24 | 0.3
children over 2 | over 24 | 0.6

Other information

- tamper evident: do not use if printed seal under cap is broken or missing
- store at room temperature
- do not freeze
- see bottom panel for lot number and expiration date

Inactive ingredients

carboxymethylcellulose sodium, citric acid, flavor, microcrystalline cellulose, polysorbate 60, potassium sorbate, purified water, sodium benzoate, sorbitan monostearate, sorbitol, xanthan gum.

Questions?

1-877-307-2192

Principal Display Panel

COMPARE TO INFANT’S MYLICON® DROPS ACTIVE INGREDIENT*

Parent’s CHOICE™

Infants'

Gas Relief

Drops

Simethicone /Antigas

No Artificial Colors, Flavors or Saccharin

Dye-Free, Non-Staining Formula

1 FL. OZ. (30 mL) 100 doses

DISTRIBUTED BY: Walmart, Bentonville, AR 72716

Made in USA with domestic and imported ingredients.

Factory certified.

Syringe Enclosed. This bottle contains 100 doses (0.3mL/dose)

* This product is not manufactured or distributed by Infirst Healthcare Inc., the distributor of Infants’ Mylicon®Drops.

- IMPORTANT: Keep this carton for future reference on full labeling